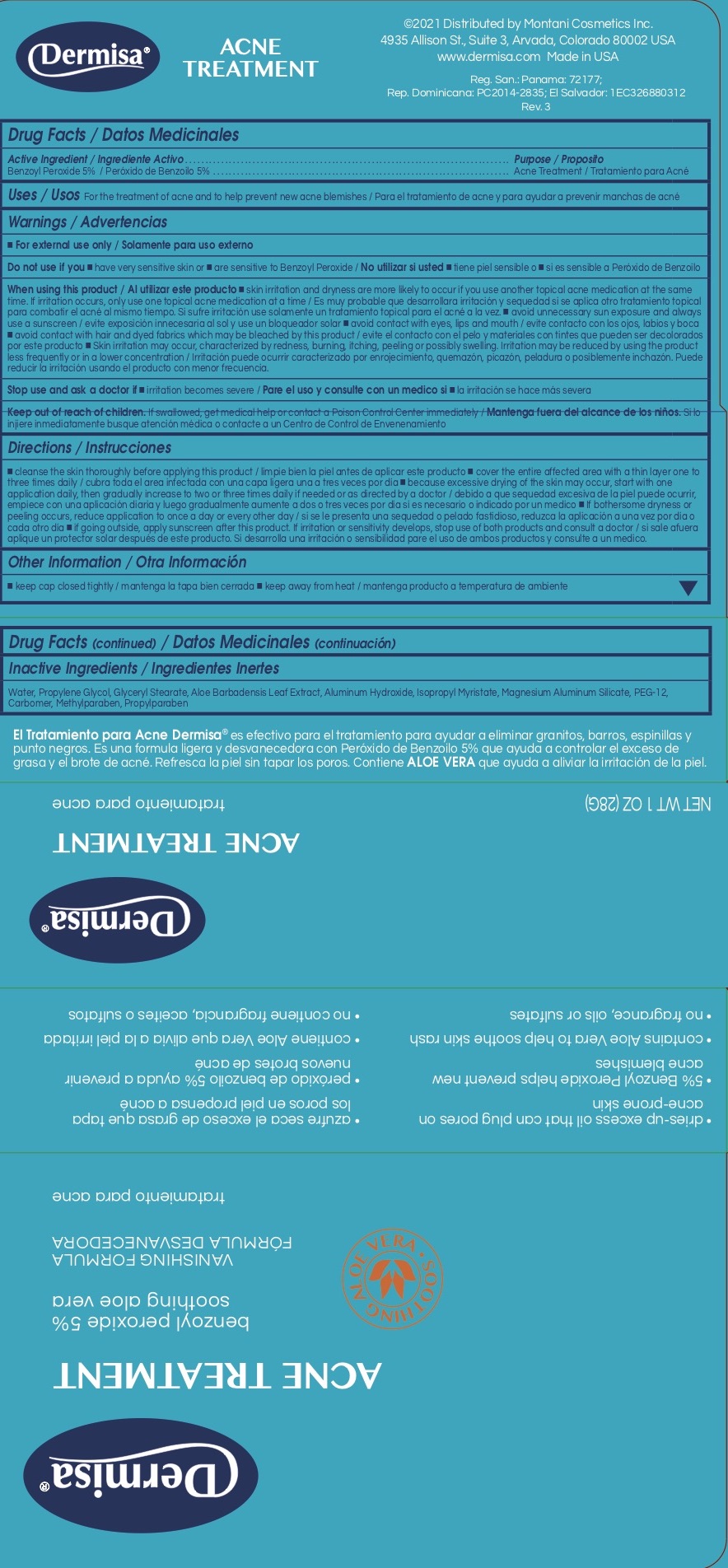 DRUG LABEL: Dermisa Acne Treatment
NDC: 68343-123 | Form: CREAM
Manufacturer: Montani Cosmetics Inc
Category: otc | Type: HUMAN OTC DRUG LABEL
Date: 20241215

ACTIVE INGREDIENTS: BENZOYL PEROXIDE 5 g/100 g
INACTIVE INGREDIENTS: POLYETHYLENE GLYCOL 600; ALOE VERA LEAF; ALUMINUM HYDROXIDE; CARBOMER 940; GLYCERYL MONOSTEARATE; ISOPROPYL MYRISTATE; MAGNESIUM ALUMINUM SILICATE; METHYLPARABEN; PROPYLENE GLYCOL; PROPYLPARABEN; WATER

Active Ingredient/Ingrediente Activo

Benzoyl Peroxide 5% /Peróxido de Benzoilo 5%

Purpose/Proposito

Acne Treatment/Tratamiento para Acné

INDICATIONS AND USAGE

Uses/Usos For the treatment of acne and to help prevent new acne blemishes / Para el tratamiento de acne y para ayudar a prevenir manchas de acné

WARNINGS

Warnings/Advertencias*For external use only / Solamente para uso externo

Do not use if you ■have very sensitive skin or are sensitive to Benzoyl Peroxide/ No utilizar si usted ■tiene pielsensible o si es sensible a Peróxido de Benzoilo

When using this product /Al utilizar este producto ■avoid unnecessary sun exposure and always use a sunscreen/evite exposición innecesaria al sol y use un bloqueador solar ■avoid contact with eyes, lips and mouth/evite contacto con los ojos, labios y boca ■avoid contact with hair and dyed fabrics which may be bleached by this product/evite el contacto con el pelo y materiales con tintes que pueden ser decolorados por este producto ■skin irritation may occur characterized by redness, burning, itching, peeling or possibly swelling. Irritation may be reduced by using the product less frequently or in a lower concentration/irritación de la piel puede ocurrir caracterizado por quemazón, enrojecimiento, picazón, peladura o posiblemente hinchazón. La irritación se puede reducer disminuyendo la frecuencia de uso del producto o usándolo en menor concentración.

Stop use and ask a doctor if ■irritation becomes severe/ Pare el uso y consulte con un medico ■si la irritación se hace más severa

Keep out of reach of children. If swallowed, get medical help or contact a Poison Control Center immediately/ Mantenga fuera del alcance de los niños. Si lo injiere inmediatamente busque atención médica o contacte a un Centro de Control de Envenenamiento

DOSAGE AND ADMINISTRATION

Directions/ Instrucciones

■Clean the skin thoroughly before applying this product/ limpie bien la piel antes de aplicar este producto ■cover the entire affected area with a thin layer one to three times daily/cobra toda el area infectada con una capa ligera una a tres veces por día ■because excessive drying of the skin may occur, start with one application daily, then gradually increase to two or three times daily if needed or as directed by a doctor/debido a que sequedad excesiva de la piel puede ocurrir, empiece con una aplicación diaria y luego, gradualmente aumente a dos o tres veces por día si es necesario o indicado por un medico ■If bothersome dryness or peeling occurs, reduce application to once a day or every other day /si se le presenta una sequedad o pelado fastidioso, reduzca la aplicación a una vez por día o cada otro día if going outside, apply sunscreen after this product. ■If irritation or sensitivity develops, stop use of both products and ask a doctor/si sale afuera aplique un protector solar después de este producto. Si desarrolla una irritación o sensibilidad pare el uso de ambos productos y consulte a un medico.

Other Information/ Otra Información

■Keep cap closed tightly / mantenga la tapa bien cerrada *Store at room temperature/mantenga producto a temperatura de ambiente

Inactive Ingredients/ Ingredientes Inertes

Aloe Vera Gel/Aloe Vera Gel, Aluminum Hydroxide/Hidroxido de Aluminio, Carbomer/Carbomer, Glyceryl Monostearate/Monoestearato de Glicerilo, IsopropylMyristate/Miristato de Isopropilo, Magnesium Aluminum Silicate/Silicato de Aluminio y Magnesio, Methylparaben/Metylparabeno, PEG 12/PEG 12, PropyleneGlycol/Propylenglicol, Propylparaben/Propilparabeno, Purified Water/Agua Purificada